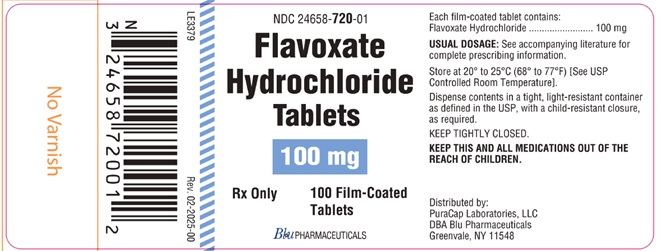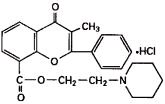 DRUG LABEL: Flavoxate Hydrochloride
NDC: 24658-720 | Form: TABLET
Manufacturer: PuraCap Laboratories LLC dba Blu Pharmaceuticals
Category: prescription | Type: HUMAN PRESCRIPTION DRUG LABEL
Date: 20251211

ACTIVE INGREDIENTS: FLAVOXATE HYDROCHLORIDE 100 mg/1 1
INACTIVE INGREDIENTS: SILICON DIOXIDE; STARCH, CORN; MAGNESIUM STEARATE; HYPROMELLOSE 2910 (50 MPA.S); POLYDEXTROSE; POLYETHYLENE GLYCOL 8000; TITANIUM DIOXIDE; TRIACETIN; DIBASIC CALCIUM PHOSPHATE DIHYDRATE

Flavoxate Hydrochloride Tablets 100 mg, Film-Coated
Rx only

DESCRIPTION

Flavoxate hydrochloride tablets contain flavoxate hydrochloride, a synthetic urinary tract spasmolytic.

Chemically, flavoxate hydrochloride is 2-piperidinoethyl 3-methyl-4-oxo-2-phenyl-4 H-1-benzopyran-8-carboxylate hydrochloride. The empirical formula of flavoxate hydrochloride is C 24H 25NO 4•HCl. The molecular weight is 427.94. The structural formula appears below.

Each tablet for oral administration contains 100 mg flavoxate hydrochloride. In addition, each tablet contains the following inactive ingredients: colloidal silicon dioxide, corn starch, dibasic calcium phosphate dihydrate, magnesium stearate, hypromellose, polydextrose, polyethylene glycol, titanium dioxide and triacetin.

CLINICAL PHARMACOLOGY

Flavoxate hydrochloride counteracts smooth muscle spasm of the urinary tract and exerts its effect directly on the muscle.

In a single study of 11 normal male subjects, the time to onset of action was 55 minutes. The peak effect was observed at 112 minutes. 57% of the flavoxate hydrochloride was excreted in the urine within 24 hours.

INDICATIONS AND USAGE

Flavoxate hydrochloride tablets are indicated for symptomatic relief of dysuria, urgency, nocturia, suprapubic pain, frequency and incontinence as may occur in cystitis, prostatitis, urethritis, urethrocystitis/urethrotrigonitis. Flavoxate hydrochloride tablets are not indicated for definitive treatment, but are compatible with drugs used for the treatment of urinary tract infections.

CONTRAINDICATIONS

Flavoxate hydrochloride is contraindicated in patients who have any of the following obstructive conditions: pyloric or duodenal obstruction, obstructive intestinal lesions or ileus, achalasia, gastrointestinal hemorrhage and obstructive uropathies of the lower urinary tract.

WARNINGS

Flavoxate hydrochloride should be given cautiously in patients with suspected glaucoma.

PRECAUTIONS

Information for Patients

Patients should be informed that if drowsiness and blurred vision occur, they should not operate a motor vehicle or machinery or participate in activities where alertness is required.

Carcinogenesis, Mutagenesis, Impairment of Fertility

Mutagenicity studies and long-term studies in animals to determine the carcinogenic potential of flavoxate hydrochloride have not been performed.

Pregnancy

Teratogenic Effects-Pregnancy Category B

Reproduction studies have been performed in rats and rabbits at doses up to 34 times the human dose and revealed no evidence of impaired fertility or harm to the fetus due to flavoxate hydrochloride. There are, however, no well-controlled studies in pregnant women. Because animal reproduction studies are not always predictive of human response, this drug should be used during pregnancy only if clearly needed.

Nursing Mothers

It is not known whether this drug is excreted in human milk. Because many drugs are excreted in human milk, caution should be exercised when flavoxate hydrochloride is administered to a nursing woman.

Pediatric Use

Safety and effectiveness in children below the age of 12 years have not been established.

ADVERSE REACTIONS

The following adverse reactions have been observed, but there are not enough data to support an estimate of their frequency.

Gastrointestinal: Nausea, vomiting, dry mouth.

CNS: Vertigo, headache, mental confusion, especially in the elderly, drowsiness, nervousness.

Hematologic: Leukopenia (one case which was reversible upon discontinuation of the drug).

Cardiovascular: Tachycardia and palpitation.

Allergic: Urticaria and other dermatoses, eosinophilia and hyperpyrexia.

Ophthalmic: Increased ocular tension, blurred vision, disturbance in eye accommodation.

Renal: Dysuria.

OVERDOSAGE

The oral LD 50 for flavoxate hydrochloride in rats is 4273 mg/kg. The oral LD 50 for flavoxate hydrochloride in mice is 1837 mg/kg.

It is not known whether flavoxate hydrochloride is dialyzable.

DOSAGE AND ADMINISTRATION

Adults and children over 12 years of age

One or two 100 mg tablets 3 or 4 times a day. With improvement of symptoms, the dose may be reduced. This drug cannot be recommended for infants and children under 12 years of age because safety and efficacy have not been demonstrated in this age group.

HOW SUPPLIED

Flavoxate hydrochloride 100 mg tablets are available as white, round biconvex, film-coated tablets, debossed “Є58” on one side and plain on the other side.

They are supplied as follows:

NDC 24658-720-01 in bottles of 100

Store at 20° - 25°C (68° - 77°F) [See USP Controlled Room Temperature]. Dispense contents in a tight, light-resistant container.

Distributed by:

PuraCap Laboratories, LLC

DBA Blu Pharmaceuticals

Greenvale, NY 11548

Rev. 02-2025-00

MF058REV02/25

OE2582

PACKAGE/LABEL PRINCIPAL DISPLAY PANEL – 100 mg 100ct

Flavoxate Hydrochloride Tablets, 100 mg

Rx Only

100 Film-Coated Tablets